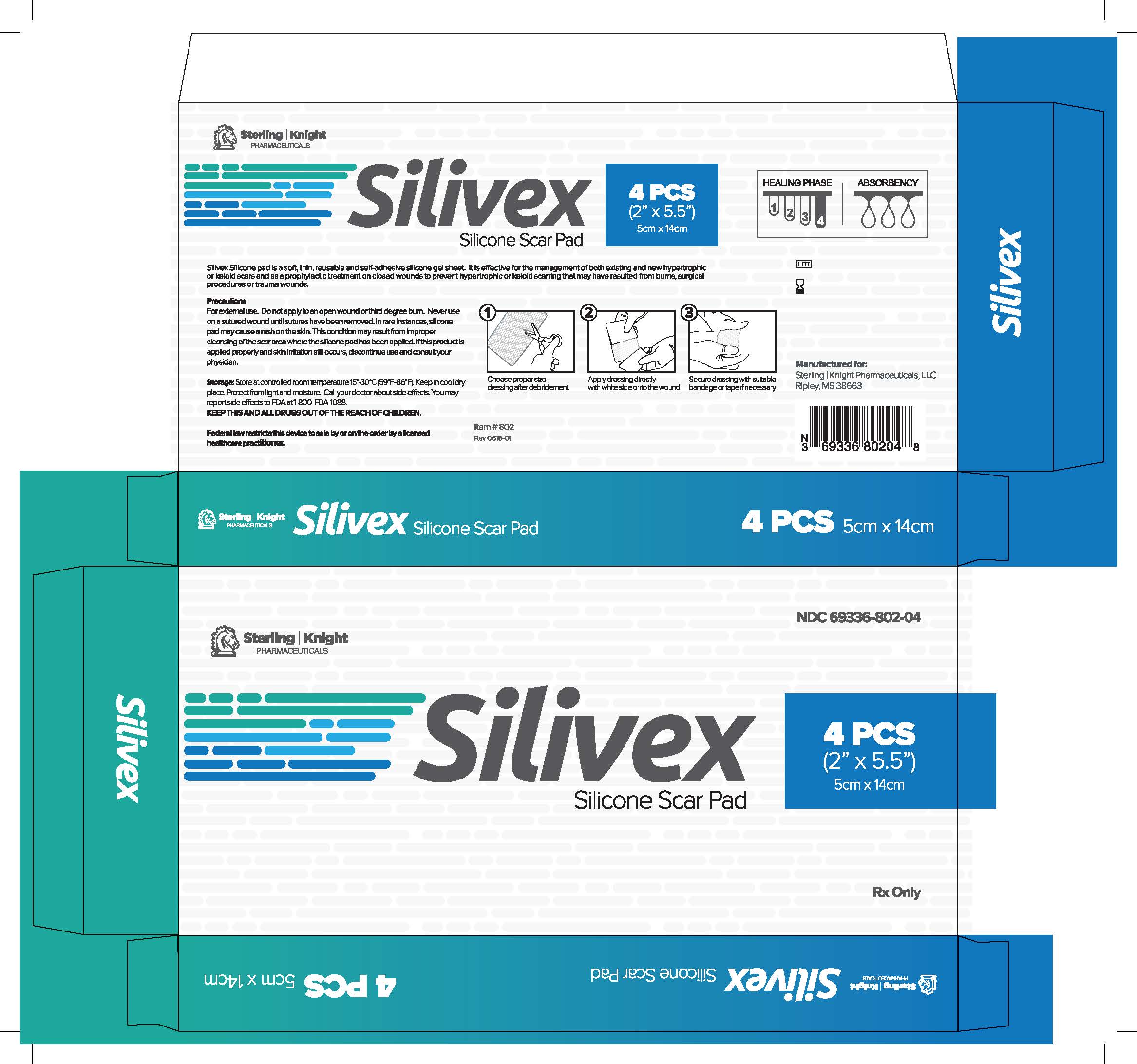 DRUG LABEL: Silivex
NDC: 69336-802
Manufacturer: Sterling-Knight Pharmaceuticals, LLC
Category: other | Type: MEDICAL DEVICE
Date: 20180919

Silivex
(Silicone Scar Pad)

Rx only

For external use only
Not for Ophthalmic use

Silivex Silicone Scar Pad Description

Silivex Silicone pad is a soft, thin, reusable and self-adhesive silicone gel sheet. It is effective for the management of both existing and new hypertrophic or keloid scars and as a prophylactic treatment on closed wounds to prevent hypertrophic or keloid scarring that may have resulted from burns, surgical procedures or trauma wounds.

Each Silivex Pad contains: Silicone gel matrix (Polydimethyl hydrogenmethyl siloxane, Polydimethylsiloxane, and Polydimethylsiloxane hydrogen terminated).

Silivex Silicone Scar Pad - Clinical Pharmacology

The exact mechanism of silicone gel in improving the appearance of scar tissue remains unknown. However, numerous mechanisms have been suggested to explain the efficacy of silicone gel, including hydration, pressure, temperature, oxygen transmission and silicone absorption. There is some evidence that the treatment affects the stratum corneum and, by reducing evaporation, restores better homeostasis in the tissue. In keloid and hypertrophic scarring, the stratum corneum allows more evaporation of water from the underlying tissue than occurs in normal skin. Silicone pads may prevent this, keeping the stratum corneum in optimal hydration and protecting the skin from environmental hazards, both of which can reduce abnormal scarring. The gel may also affect the stratum corneum by inhibiting mast cell activity, diminishing edema, vasodilatation and excessive extracellular matrix formation but the simple changes in temperature, pressure, oxygen tension and hydration produced by wound coverage probably constitute the main mechanism of action. Another hypothesis is that the effect of static electricity on silicone may influence the alignment of collagen deposition.

INDICATIONS AND USES

For external use only. Temporary use in the management of both existing and new hypertrophic or keloid scars. Temporary use as a prophylactic treatment on closed wounds to prevent hypertrophic or keloid scarring. Do not use on open wounds.

CONTRAINDICATIONS

Silivex Pad is contraindicated in patients with known hypersensitivity to silicone or any of the listed ingredients.

WARNINGS

For external use. Do not apply to an open wound or third degree burn. Never use on a sutured wound until sutures have been removed. In rare instances, silicone pad may cause a rash on the skin. This condition may result from improper cleansing of the scar area where the silicone pad has been applied. If this product is applied properly and skin irritation still occurs, discontinue use and consult your physician.

PRECAUTIONS

Stop use and ask a doctor if irritation develops. In rare instances, silicone sheets may cause a rash on the skin. This condition may result from improper cleansing of the scar area where the silicone pad has been applied. If this product is applied properly and skin irritation still occurs, discontinue use and consult your physician. If ingested, get medical help or contact Poison Control Center right away. KEEP THIS AND ALL MEDICATION OUT OF THE REACH OF CHILDREN.

Call your doctor about side effects. You may report side effects to FDA at 1-800-FDA-1088. KEEP THIS AND ALL DRUGS OUT OF THE REACH OF CHILDREN.

Caution:

Federal law restricts this device to sale by or on the order by a licensed healthcare practitioner.

ADVERSE REACTIONS

Rarely the Pads may cause transient redness stinging, burning or irritation and normally disappear on discontinuing the medication.

DOSAGE AND ADMINISTRATION

1. Wash your hands and the scar area with soap and water. Dry thoroughly.
2. Cut the Silivex Pad to fit the scar area so that the edges of the gel pad extend at least 1/4'' beyond the scar on all sides.
3. Peel of the strip and place the sticky side of the pad directly onto the scar. Leave on for 8-12 hours per day then remove. Do not discard the mylar release strip.
4. When not wearing the pad, place the gel pad (sticky side) back onto the mylar release strip.
5. Discard the pad and replace with a new one every 7 days.

HOW SUPPLIED

Silivex Pad is supplied in:

Four (4) Large Non-Sterile Silicone Gel Pad – 2” x 5.5” in 1 Carton, NDC 69336-802-04
Two (2) Large Non-Sterile Silicone Gel Pad – 2” x 5.5” in 1 Carton, NDC 69336-802-02

STORAGE

Store at controlled room temperature 15°-30°C (59°F-86°F). Keep in cool dry place. Protect from light and moisture.

Distributed By:

Sterling-Knight Pharmaceuticals, LLC
Ripley, MS 38663
Rev 0618-1

PRINCIPAL DISPLAY PANEL - 4 Pad Pouch Carton

Sterling-Knight Pharmaceuticals, LLC
Ripley, MS 38663
Rev 0618-1

Silivex

Silicone Scar Pad

Prescription Only